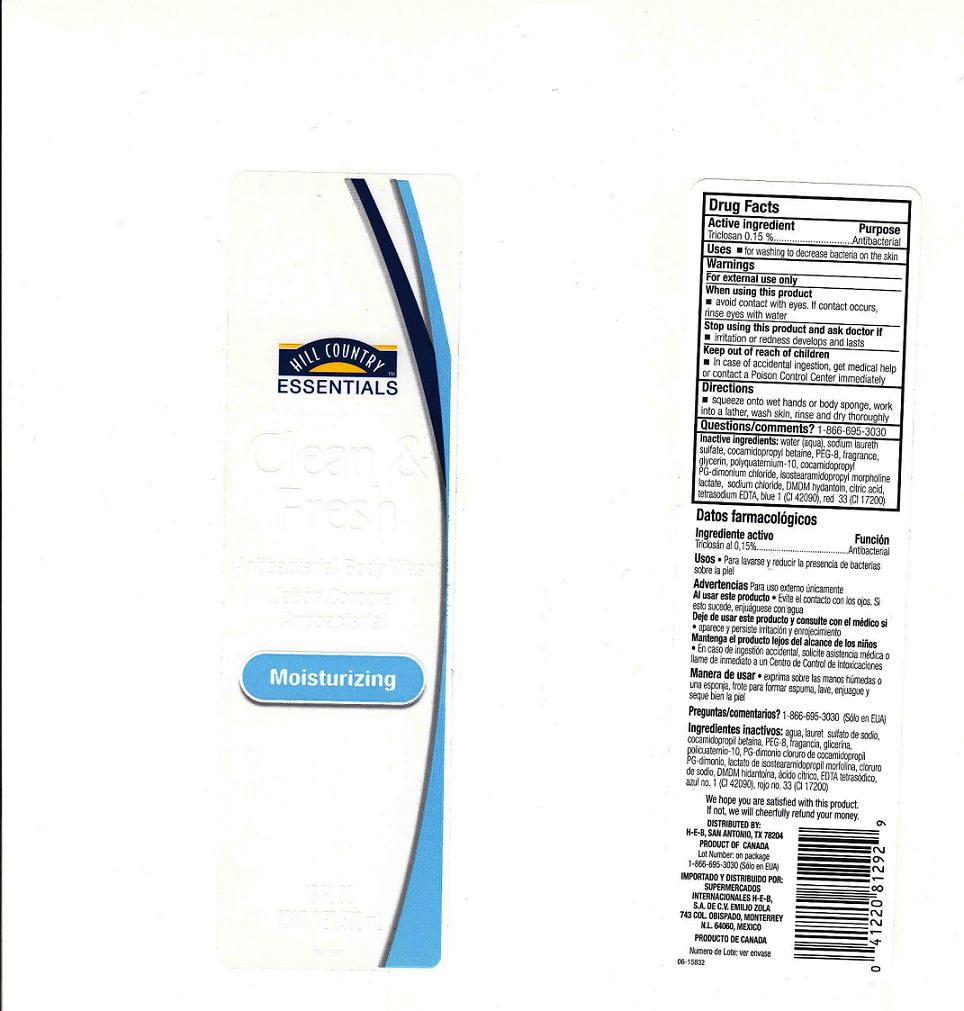 DRUG LABEL: Clean and Refresh Body Wash
NDC: 37808-801 | Form: SOAP
Manufacturer: HEB
Category: otc | Type: HUMAN OTC DRUG LABEL
Date: 20100922

ACTIVE INGREDIENTS: TRICLOSAN 0.15 mL/100 mL

Drug Facts Box - Back Panel

Active Ingredient

Triclosan 0.15%

Purpose

Antibacterial

Warnings

For external use only.

When using this product

- Avoid contact with eyes. If contact occurs, rinse with water.

Stop using this product and ask doctor if

- Irritation and redness develop.

Keep out of reach of children.

In case of accidental ingestion, get medical help or contact a Poison Control Center immediately.

Questions?

Call: 1-866-695-3030

Use

For washing to decrease bacteria on skin.

Directions

- squeeze onto wet hands or body sponge

- work into a lather

- wash skin, rinse, and dry thoroughly

Inactive Ingredients

Water (Aqua), Sodium Laureth Sulfate, Cocamidopropyl Betaine, PEG-8, Fragrance (Parfum), Glycerin, Isostearoamidopropyl Morpholine Lactate, Polyquaternium-10, Cocamidopropyl PG-Dimonium Chloride, DMDM Hydantoin, Citric Acid, Tetrasodium EDTA, Sodium Chloride, Blue 1 (Cl 42090), Red 33 (Cl 17200).

PACKAGE FRONT AND BACK LABELS

18OZ FRONT AND BACK LABELS: hcf18.jpg